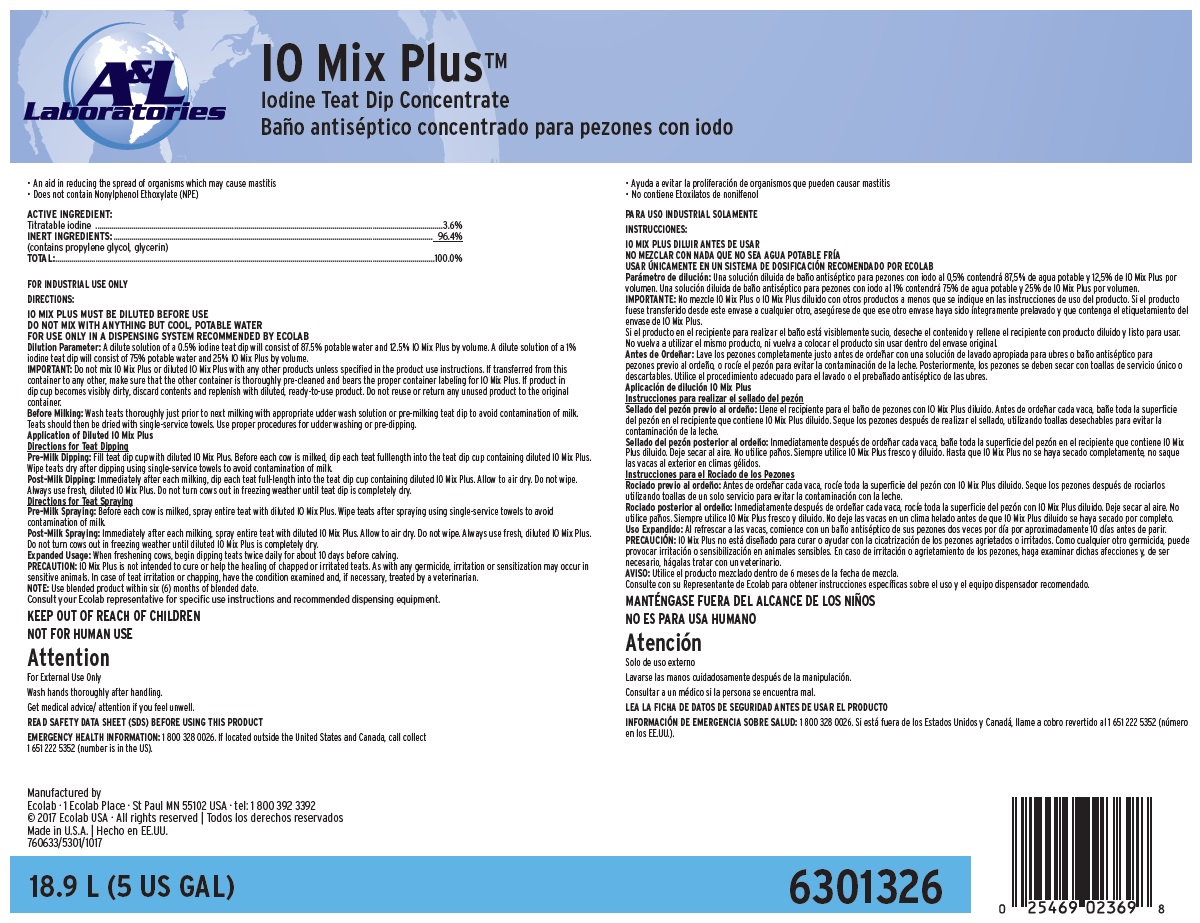 DRUG LABEL: IO Mix Plus
NDC: 47593-531 | Form: SOLUTION
Manufacturer: Ecolab Inc.
Category: animal | Type: OTC ANIMAL DRUG LABEL
Date: 20250918

ACTIVE INGREDIENTS: IODINE 36 mg/1 mL
INACTIVE INGREDIENTS: WATER; GLYCERIN; PROPYLENE GLYCOL

SAFE HANDLING WARNING

FOR INDUSTRIAL USE ONLY

KEEP OUT OF REACH OF CHILDREN

NOT FOR HUMAN USE

Attention

For External Use Only

Wash hands thoroughly after handling.

Get medical advice/ attention if you feel unwell.

DIRECTIONS:

IO MIX PLUS MUST BE DILUTED BEFORE USE

DO NOT MIX WITH ANYTHING BUT COOL, POTABLE WATER

FOR USE ONLY IN A DISPENSING SYSTEM RECOMMENDED BY ECOLAB

Dilution Parameter: A dilute solution of a 0.5% iodine teat dip will consist of 87.5% potable water and 12.5% IO Mix Plus by volume. A dilute solution of a 1% iodine teat dip will consist of 75% potable water and 25% IO Mix Plus by volume.

IMPORTANT: Do not mix IO Mix Plus or diluted IO Mix Plus with any other products unless specified in the product use instructions. If transferred from this container to any other, make sure that the other container is thoroughly pre-cleaned and bears the proper container labeling for IO Mix Plus. If product in dip cup becomes visibly dirty, discard contents and replenish with diluted, ready-to-use product. Do not reuse or return any unused product to the original container.

Before Milking: Wash teats thoroughly just prior to next milking with appropriate udder wash solution or pre-milking teat dip to avoid contamination of milk. Teats should then be dried with single-service towels. Use proper procedures for udder washing or pre-dipping.

Application of Diluted IO Mix Plus

Directions for Teat Dipping

Pre-Milk Dipping: Fill teat dip cup with diluted IO Mix Plus. Before each cow is milked, dip each teat fulllength into the teat dip cup containing diluted IO Mix Plus. Wipe teats dry after dipping using single-service towels to avoid contamination of milk.

Post-Milk Dipping: Immediately after each milking, dip each teat full-length into the teat dip cup containing diluted IO Mix Plus. Allow to air dry. Do not wipe. Always use fresh, diluted IO Mix Plus. Do not turn cows out in freezing weather until teat dip is completely dry.

Directions for Teat Spraying

Pre-Milk Spraying: Before each cow is milked, spray entire teat with diluted IO Mix Plus. Wipe teats after spraying using single-service towels to avoid contamination of milk.

Post-Milk Spraying: Immediately after each milking, spray entire teat with diluted IO Mix Plus. Allow to air dry. Do not wipe. Always use fresh, diluted IO Mix Plus. Do not turn cows out in freezing weather until diluted IO Mix Plus is completely dry.

Expanded Usage: When freshening cows, begin dipping teats twice daily for about 10 days before calving.

PRECAUTION: IO Mix Plus is not intended to cure or help the healing of chapped or irritated teats. As with any germicide, irritation or sensitization may occur in sensitive animals. In case of teat irritation or chapping, have the condition examined and, if necessary, treated by a veterinarian.

NOTE: Use blended product within six (6) months of blended date.

Consult your Ecolab representative for specific use instructions and recommended dispensing equipment.

OTHER SAFETY INFORMATION

READ SAFETY DATA SHEET (SDS) BEFORE USING THIS PRODUCT

EMERGENCY HEALTH INFORMATION: 1 800 328 0026. If located outside the United States and Canada, call collect 1 651 222 5352 (number is in the US).

Representative label and principal display panel

A&L Laboratories

IO Mix Plus™

Iodine Teat Dip Concentrate

• An aid in reducing the spread of organisms which may cause mastitis

• Does not contain Nonylphenol Ethoxylate (NPE)

ACTIVE INGREDIENT:

Titratable iodine ......................................................................3.6%

INERT INGREDIENTS:............................................................... 96.4%

(contains propylene glycol, glycerin)

TOTAL:......................................................................................100.0%

18.9 L (5 US GAL)

6301326

Manufactured by

Ecolab · 1 Ecolab Place · St Paul MN 55102 USA · tel: 1 800 392 3392

© 2017 Ecolab USA · All rights reserved

Made in U.S.A.

760633/5301/1017